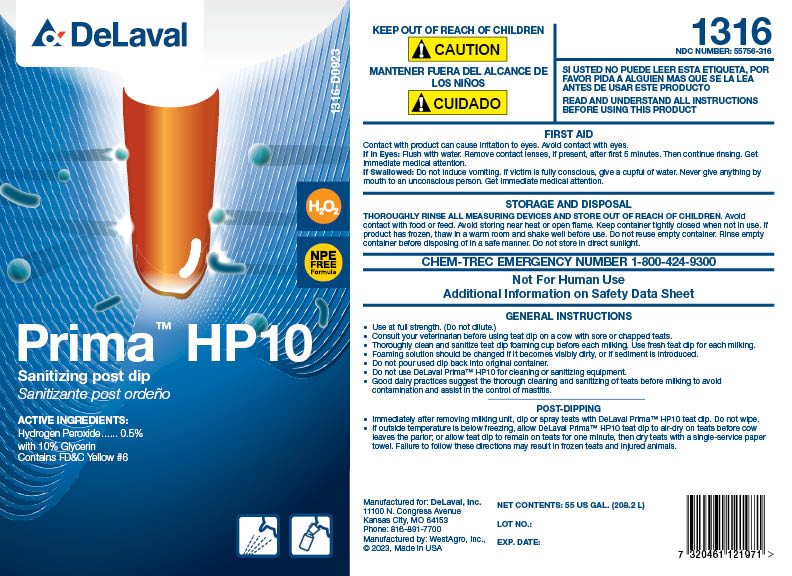 DRUG LABEL: Prima HP10
NDC: 55756-316 | Form: SOLUTION
Manufacturer: DeLaval
Category: animal | Type: OTC ANIMAL DRUG LABEL
Date: 20230907

ACTIVE INGREDIENTS: HYDROGEN PEROXIDE 5 g/1 L
INACTIVE INGREDIENTS: WATER; HYDROXYETHYL CELLULOSE (3000 MPA.S AT 1%); DODECYLBENZENESULFONIC ACID; LACTIC ACID; SODIUM HYDROXIDE; SALICYLIC ACID; GLYCERIN; DOCUSATE SODIUM; ETIDRONIC ACID; BENZYL ALCOHOL; FD&C YELLOW NO. 6

PRIMA HP10

PURPOSE

Prima HP10

Sanitizing post dip

Sanitizante post ordeno

ACTIVE INGREDIENTS:

Hydrogen Peroxide......0.5%

with 10% Glycerin

Contains FD&C Yellow #6

H2O2

NPE FREE Formula

KEEP OUT OF REACH OF CHILDREN

! CAUTION

MANTINER FUERA DEL ALCANCE DE LOS NINOS

! CUIDADO

SI USTED PUEDE LEER ESTA ETIQUETA, POR FAVOR PIDA A ALGUIEN MAS QUE SE LA LEA ANTES DE USAR ESTE PRODUCTO

READ AND UNDERSTAND ALL INSTRUCTIONS BEFORE USING THIS PRODUCT

FIRST AID

Contact with product can cause irritation to eyes. Avoid contact with eyes.

If in Eyes: Flush with water. Remove contact lenses, if present, after first 5 minutes. Then continue rinsing. Get immediate medical attention.

If Swallowed: Do not induce vomiting. If victim is fully conscious, give a cupful of water. Never give anything my mouth to an unconscious person. Get immediate medical attention.

STORAGE AND DISPOSAL

THOROUGHLY RINSE ALL MEASURING DEVICES AND STORE OUT OF REACH OF CHILDREN. Avoid contact with food or feed. Avoid storing near heat or open flame. Keep container tightly closed when not in use. If product has frozen, thaw in a warm room and shake well before using. Do not reuse empty container. Rinse empty container before disposing of in a safe manner. Do not store in direct sunlight.

CHEM-TREC EMERGENCY NUMBER 1-800-424-9300

Not For Human Use

Additional Information on Safety Data Sheet

DOSAGE AND ADMINISTRATION

GENERAL INSTRUCTIONS

- Use at full strength. (Do not dilute.)
- Consult your veterinarian before using teat dip on a cow with sore or chapped teats.
- Thoroughly clean and sanitize teat dip foaming cup before each milking. Use fresh teat dip for each milking.
- Foaming solution should be changed if it becomes visibly dirty, or if sediment is introduced.
- Do not pour used dip back into original container.
- Do not use DeLaval Prima™ HP10 for cleaning or sanitizing equipment.
- Good dairy practices suggest the thorough cleaning and sanitizing of teats before milking to avoid contamination and assist in the control of mastitis.

POST-DIPPING

- Immediately after removing milking unit, dip or spray teats with DeLaval Prima™ HP10 teat dip. Do not wipe.
- If outside temperature is below freezing, allow DeLaval Prima HP10 teat dip to air-dry on teats before cow leaves the parlor; or allow teat dip to remain on teats for one minute, then dry teats with a single-service paper towel. Failure to follow these directions may result in frozen teats and injured animals.

NET CONTENTS: US GAL.

LOT NO.:

EXP. DATE:

Manufactured for: DeLaval, Inc.

11100 N. Congress Avenue

Kansas City, MO 64153

Phone: 816-891-7700

Manufactured by: WestAgro, Inc.,

© 2023, Made in USA

PACKAGE LABEL

Add image transcription here...

Add image transcription here...